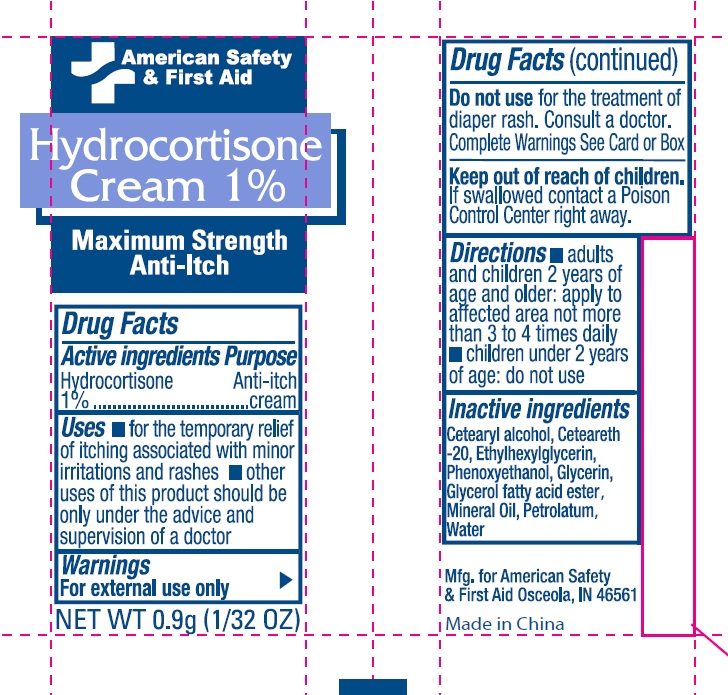 DRUG LABEL: American Safety and First Aid
NDC: 71927-031 | Form: CREAM
Manufacturer: Orazen Inc
Category: otc | Type: HUMAN OTC DRUG LABEL
Date: 20260104

ACTIVE INGREDIENTS: HYDROCORTISONE ACETATE 10 mg/1 g
INACTIVE INGREDIENTS: PETROLATUM; POLYOXYL 20 CETOSTEARYL ETHER; CETOSTEARYL ALCOHOL; ETHYLHEXYLGLYCERIN; PHENOXYETHANOL; GLYCERIN; MINERAL OIL; WATER

71927-031 American Safety & First Aid
Hydrocortisone Cream 1%

Active Ingredient

Hydrocortisone 1%

Purpose

Anti-Itch Cream

Uses

- for the temporary relief of itching associated with minor irritations and rashes
- Other uses of this product should be only under the advice and supervision of a doctor

Warnings

For external use only

Do not use

for the treatment of diaper rash. Consult a doctor. Complete Warnings See Card or Box

Keep out of reach of children.

If swallowed contact a Poison Control Center right away.

Directions

- adults and children 2 years of age and older :apply to affected area not more than 3 to 4 times daily
- children under 2 years of age: do not use

Inactive Ingredients

Cetearyl alcohol, Ceteareth-20, Ethylhexyglycerin, Phenoxyethanol, Glycerin, Glycerol fatty acid ester, Mineral Oil, Petrolatum, Water